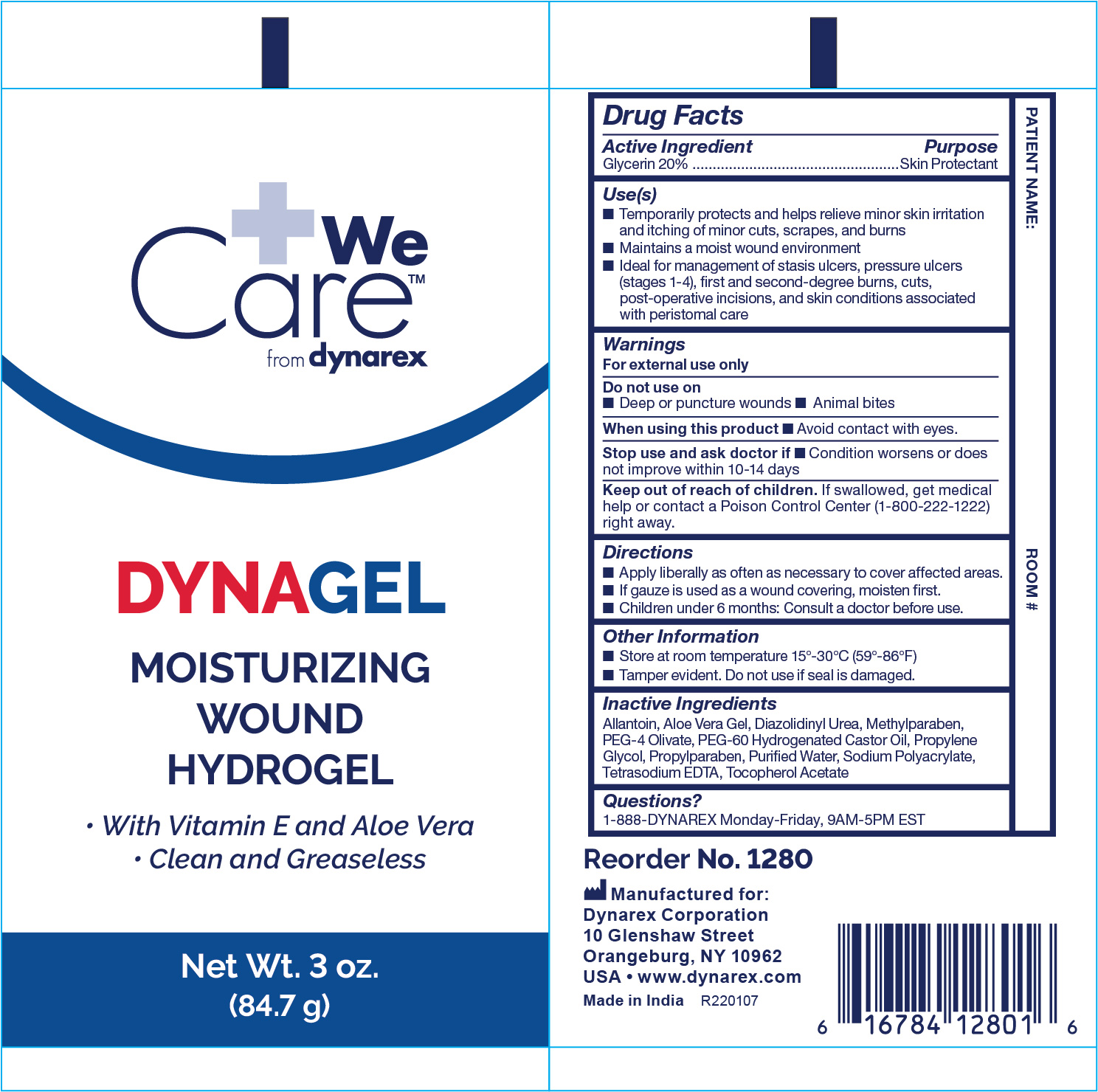 DRUG LABEL: Dynarex Hydrogel
NDC: 67777-233 | Form: GEL
Manufacturer: Dynarex Corporation
Category: otc | Type: HUMAN OTC DRUG LABEL
Date: 20241120

ACTIVE INGREDIENTS: GLYCERIN 20 g/100 g
INACTIVE INGREDIENTS: METHYLPARABEN; PROPYLENE GLYCOL; POLYOXYL 60 HYDROGENATED CASTOR OIL; PROPYLPARABEN; WATER; EDETATE SODIUM; ALPHA-TOCOPHEROL ACETATE; ALLANTOIN; ALOE VERA LEAF; DIAZOLIDINYL UREA; SODIUM POLYACRYLATE (8000 MW)

1280 DynaGel Moisturizing Wound Hydrogel NDC 67777-233-01

Active Ingredient

Active Ingredient Purpose

Glycerin 20.0% Skin Protectant

Purpose

For dressing and management of stasis ulcers, pressure ulcers (stages I-IV) 1st and 2nd degree burns, cuts abrasions, skin irritations, post operative incisions, and skin conditions associated with peristomal care.

Warnings

- If condition worsens or does not improve within 10-14 days, consult a physician.
- Keep this and all medications out of the reach of children.
- Follow directions for use.

Dosage & Administration Dynarex Hydrogel

- Apply Wound Gel liberally to cover involved areas; apply as often as necessary.
- If gauze is used as a wound covering, moisten first.

Keep out of reach of children

- KEEP THIS AND ALL MEDICATIONS OUT OF THE REACH OF CHILDREN

Indications and Usage:

Use:

- For dressing and management of stasis ulcers,
- pressure ulcers (stages I-IV)
- 1st and 2nd degree burns,
- cuts abrasions,
- skin irritations,
- post operative incisions,
- and skin conditions associated with peristomal care.

Inactive Ingredient

Inactive ingredients: Allantoin, Aloe Vera Gel, Diazolidinyl Urea, Methyparaben, PEG-4 Olivate, PEG-60 Hydrogenated Castor Oil, Propylene Glycol, Propylparaben, Purified Water, Sodium Polyacrylate, Tetrasodium EDTA, Tocopherol Acetate.